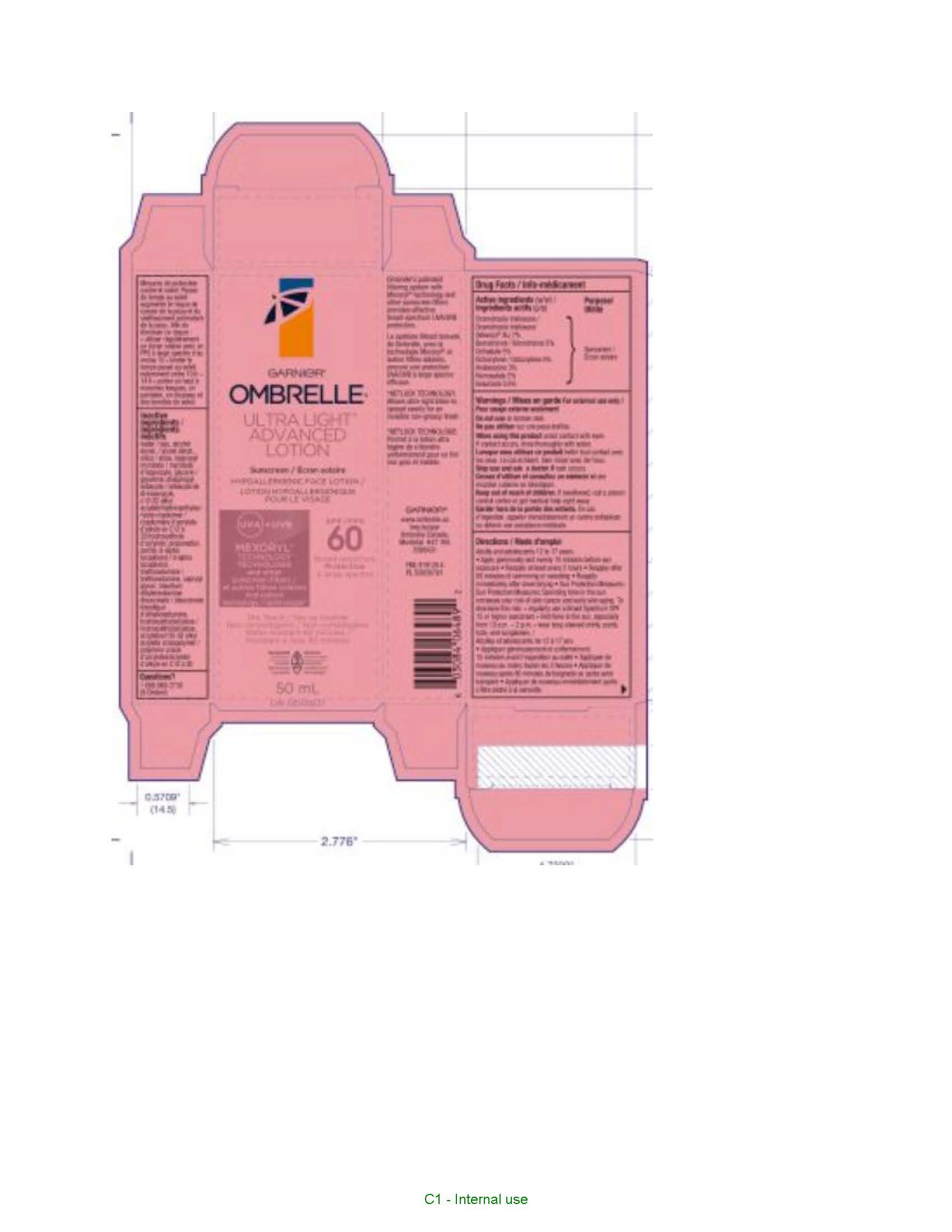 DRUG LABEL: Garnier Ombrelle Ultra Light Advanced 60 Face Sunscreen
NDC: 49967-046 | Form: LOTION
Manufacturer: L'OREAL USA PRODUCTS INC
Category: otc | Type: HUMAN OTC DRUG LABEL
Date: 20260107

ACTIVE INGREDIENTS: AVOBENZONE 30 mg/1 mL; DROMETRIZOLE TRISILOXANE 70 mg/1 mL; HOMOSALATE 20 mg/1 mL; OCTISALATE 50 mg/1 mL; OCTOCRYLENE 50 mg/1 mL; BEMOTRIZINOL 50 mg/1 mL; ENSULIZOLE 5 mg/1 mL
INACTIVE INGREDIENTS: WATER; ALCOHOL; SILICON DIOXIDE; ISOPROPYL MYRISTATE; GLYCERIN; DIISOPROPYL SEBACATE; PROPANEDIOL; PERLITE; TOCOPHEROL; TROLAMINE; CAPRYLYL GLYCOL; HYDROXYETHYL CELLULOSE, UNSPECIFIED; PENTYLENE GLYCOL; BUTYLENE GLYCOL; CITRIC ACID MONOHYDRATE

Drug Facts

Active ingredients

DROMETRIZOLE TRISILOXANE 7%
OCTOCRYLENE 5%
BEMOTRIZINOL 5%
OCTISALATE 5%
AVOBENZONE 3%
HOMOSALATE 2%
ENSULIZOLE 0.50%

Warnings

For external use only. Do not use on broken skin. When using this product avoid contact witheyes. If contact occurs, rinse thoroughlly with water. Stop use and ask a doctor if rash occurs. Keep out of reach of children. If swallowed get medical help or contact a poison control center right away.

Directions

Adults and adolescents 12 to 17 years.
Apply generously and evenly 15 minutes before sun exposure. Reapply at least every 2 hours. Reapply after 80 minutes of swimming or sweating. Reapply immediately after towel drying. Sun Protection Measures: Spending time in the sun increases your risk of skin cancer and early skin aging. To decrease this risk: regularly use a Broad Spectrum SPF 15 or higher sunscreen. Limit time in the sun, especially from 10 a.m. – 2 p.m. Wear long-sleeve shirts, pants, hats and sunglasses.

Inactive ingredients

wwater, alcohol denat., silica, isopropyl myristate, glycerin, diisopropyl sebacate, propanediol, c12-22 alkyl acrylate/hydroxyethylacrylate copolymer, perlite, tocopherol, triethanolamine, caprylyl glycol, hydroxyethylcellulose, acrylates/c10-30 alkyl acrylate crosspolymer, pentylene glycol, butylene glycol, citric acid